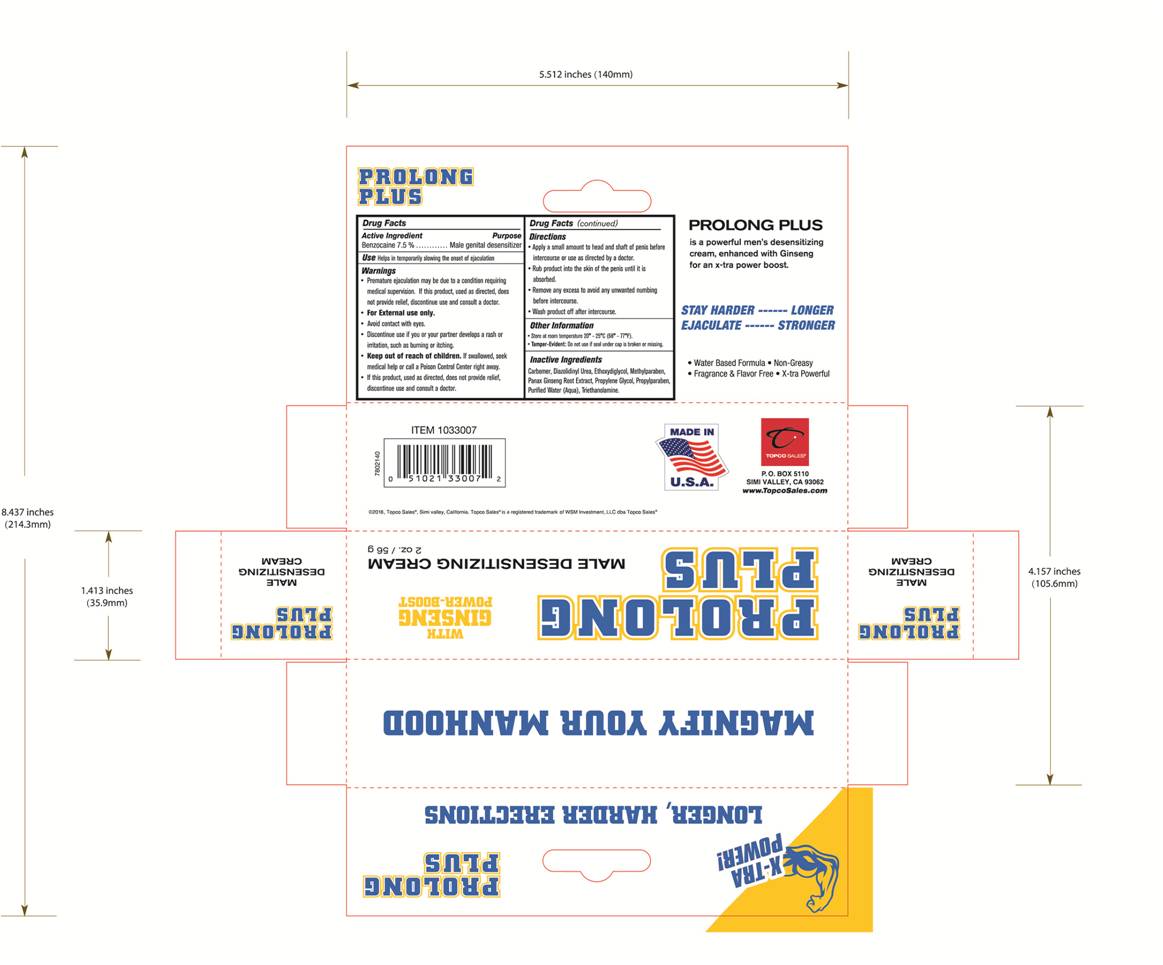 DRUG LABEL: Prolong Plus
NDC: 69797-104 | Form: CREAM
Manufacturer: WSM Investment LL. Topco Sales
Category: otc | Type: HUMAN OTC DRUG LABEL
Date: 20171219

ACTIVE INGREDIENTS: BENZOCAINE 4.2 g/56 g
INACTIVE INGREDIENTS: WATER; CARBOMER INTERPOLYMER TYPE A (ALLYL SUCROSE CROSSLINKED); PROPYLENE GLYCOL; TROLAMINE; METHYLPARABEN; DIAZOLIDINYL UREA; PROPYLPARABEN; AMERICAN GINSENG; DIETHYLENE GLYCOL MONOETHYL ETHER

ACTIVE INGREDIENT

Benzocaine - 7.5%

PURPOSE

Male Genital Desensitizer

INDICATIONS AND USAGE

Helps in temporarily slowing the onset of ejaculation.

WARNINGS

- Premature ejaculation may be due to a condition requiring medical supervision. If this product, used as directed, does not provide relief, discontinue use and consult a doctor.
- For external use only.
- Avoid contact with eyes.
- Discontinue use if you or your partner develops rash or irritation, such as burning or itching.

- Keep out of reach of children. If swallowed, seek medical help or call a Poison Control Center right away.
- If this product, used as directed, does not provide relief, discontinue use and consult a doctor.

DOSAGE AND ADMINISTRATION

- Apply a small amount to head and shaft of penis before intercourse or use as directed by a doctor.
- Rub product into the skin of the penis until it is absorbed.
- Remove any excess to avoid any unwanted numbing before intercourse.
- Wash product off after intercourse.

OTHER SAFETY INFORMATION

- Store at room temperature 20°-25°C (68°-77°F).
- Tamper-Evident: Do not use if seal under cap is broken or missing.

INACTIVE INGREDIENT

Carbomer, Diazolidinyl Urea, Ethoxydiglycol, Methylparaben, Panax Ginseng Root Extract, Propylene Glycol, Propylparaben, Purified Water (Aqua), Triethanolamine.